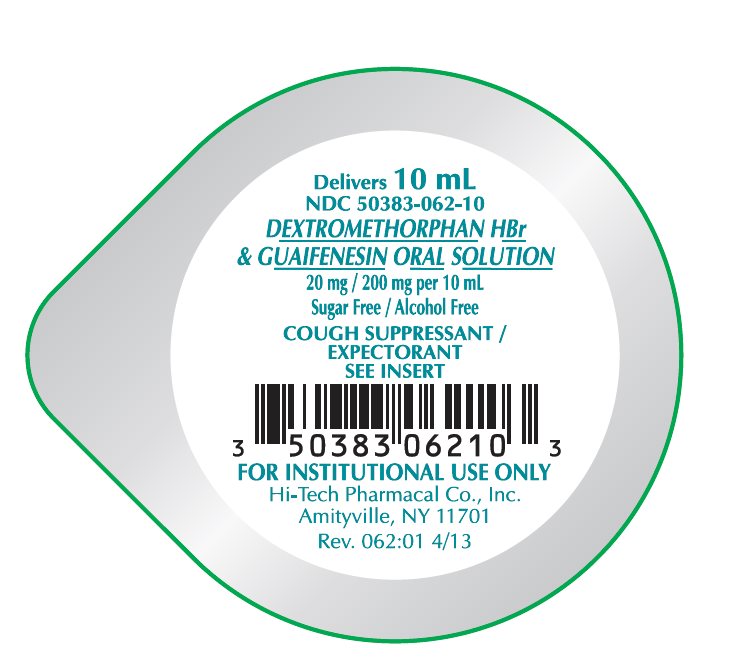 DRUG LABEL: Dextromethorphan HBr and Guaifenesin
NDC: 50383-062 | Form: SOLUTION
Manufacturer: Akorn
Category: otc | Type: HUMAN OTC DRUG LABEL
Date: 20220308

ACTIVE INGREDIENTS: DEXTROMETHORPHAN HYDROBROMIDE 10 mg/5 mL; GUAIFENESIN 100 mg/5 mL
INACTIVE INGREDIENTS: ACESULFAME POTASSIUM; ASPARTAME; HYPROMELLOSE 2910 (4000 MPA.S); MENTHOL, UNSPECIFIED FORM; METHYLPARABEN; POTASSIUM SORBATE; WATER; ANHYDROUS CITRIC ACID

Drug Facts

Active ingredient

Each 5 mL (1 teaspoonful) contains:

Dextromethorphan HBr ................................10 mg

Guaifenesin ................................................100 mg

Inactive ingredients

Acesulfame potassium, artificial cherry & vanilla flavor, aspartame, hypromellose, menthol, methylparaben, potassium sorbate, purified water. Citric acid may be used to adjust pH.

Purpose

Cough Suppressant

Expectorant

Uses

- temporarily relieves cough
- helps loosen phlegm (mucus) and thin bronchial secretions to rid bronchial passageways of bothersome mucus

Warnings

Do not use

if you are now taking a prescription monoamine oxidase inhibitor (MAOI) (certain drugs for depression, psychiatric or emotional conditions, or Parkinson’s disease), or for two weeks after stopping the MAOI drug. If you do not know if your prescription drug contains an MAOI, ask a doctor or pharmacist before taking this product.

Ask a doctor before use if you have

- a cough that occur with too much phlegm (mucus)
- a chronic cough that lasts or as occurs with smoking, asthma, chronic bronchitis, or emphysema

Stop use and ask a doctor if

- a cough lasts more than 7 days, comes back, or occurs with fever, rash, or headache that lasts
These could be signs of a serious condition.

If pregnant or breast-feeding,

ask a health professional before use.

Keep out of reach of children.

In case of overdose, get medical help or contact a Poison Control Center right away.

Professional note: Guaifenesin has been shown to produce a color interference with certain clinical laboratory determinations of 5- hydroxyindoleacetic acid (5-HIAA) and vanillylmandelic acid (VMA).

Directions

- take every 4 hours
- do not exceed 6 doses in 24 hours

Age | Dose
Adults & children 12 years & over | 10 mL (2 teaspoonfuls)
Children 6 years to under 12 years | 5 mL (1 teaspoonful)
Children 2 years to under 6 years | 2.5 mL (1/2 teaspoonful)
Children under 2 years | Ask a doctor

How Supplied: Dextromethorphan HBr and Guaifenesin Oral Solution is a clear viscous liquid with a slight cherry odor supplied in the following oral dosage forms: 5 mL unit dose, 10 mL unit dose in trays of 10 and 4 fl. oz. (118 mL) bottle

Phenylketonurics: contains phenylalanine 8.4 mg per teaspoonful (5 mL)

Storage: Keep tightly closed. Store at controlled room temperature 20-25° C (68-77°F). [See USP] Protect from light.

QUESTIONS OR COMMENTS?

Call 1-800-262-9010.

Hi-Tech Pharmacal Co., Inc.

Amityville, NY 11701

Rev.062:01 4/13

MG #29851

Package/Label Principal Display Panel

Delivers 10 mL

NDC 50383-062-10

DEXTROMETHORPHAN HBr & GUAIFENESIN ORAL SOLUTION

20 mg/200 mg per 10 mL

Sugar Free/Alcohol Free

COUGH SUPPRESSANT/EXPECTORANT

SEE INSERT

FOR INSTITUTIONAL USE ONLY

Hi-Tech Pharmacal Co., Inc.

Amityville, NY 11701

Rev. 062:01 4/13